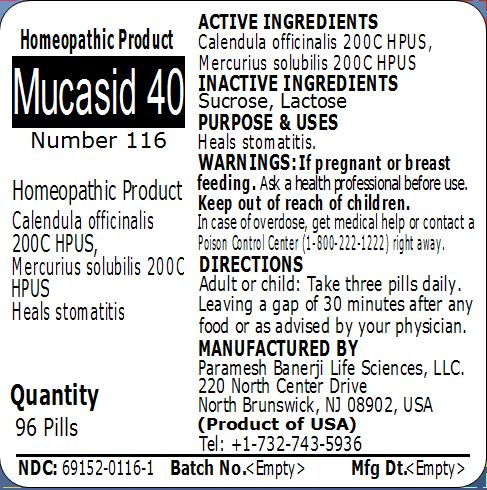 DRUG LABEL: Mucasid 40 Number 116
NDC: 69152-0116 | Form: PELLET
Manufacturer: Paramesh Banerji Life Sciences LLC
Category: homeopathic | Type: HUMAN OTC DRUG LABEL
Date: 20150314

ACTIVE INGREDIENTS: CALENDULA OFFICINALIS FLOWERING TOP 200 [hp_C]/1 1; MERCURIUS SOLUBILIS 200 [hp_C]/1 1
INACTIVE INGREDIENTS: SUCROSE; LACTOSE

Active Ingredients

Calendula officinalis 200C HPUS, Mercurius solubilis 200C HPUS

Inactive Ingredients

Sucrose, Lactose

Purpose

Heals stomatitis

Uses

Heals stomatitis

Warnings

If pregnant or breast feeding ask a health professional before use.

Keep out of reach of children. In case of overdose, get medical help or contact a Poison Control Center (1-800-222-1222) right away.

Direction

Adult or child: Take three pills daily. Leaving a gap of 30 minutes after any food or as advised by your physician.

Manufactured by

Paramesh Banerji Life Sciences, LLC

220 North Center Drive

North Brunswick, NJ 08902, USA

Product of USA

Tel: +1-732-743-5936

Principal Display Panel

Homeopathic Product

Mucasid 40

Number 116

Homeopathic Product

Calendula officinalis 200C HPUS, Mercurius solubilis 200C HPUS

Heals stomatitis

Quantity

96 Pills